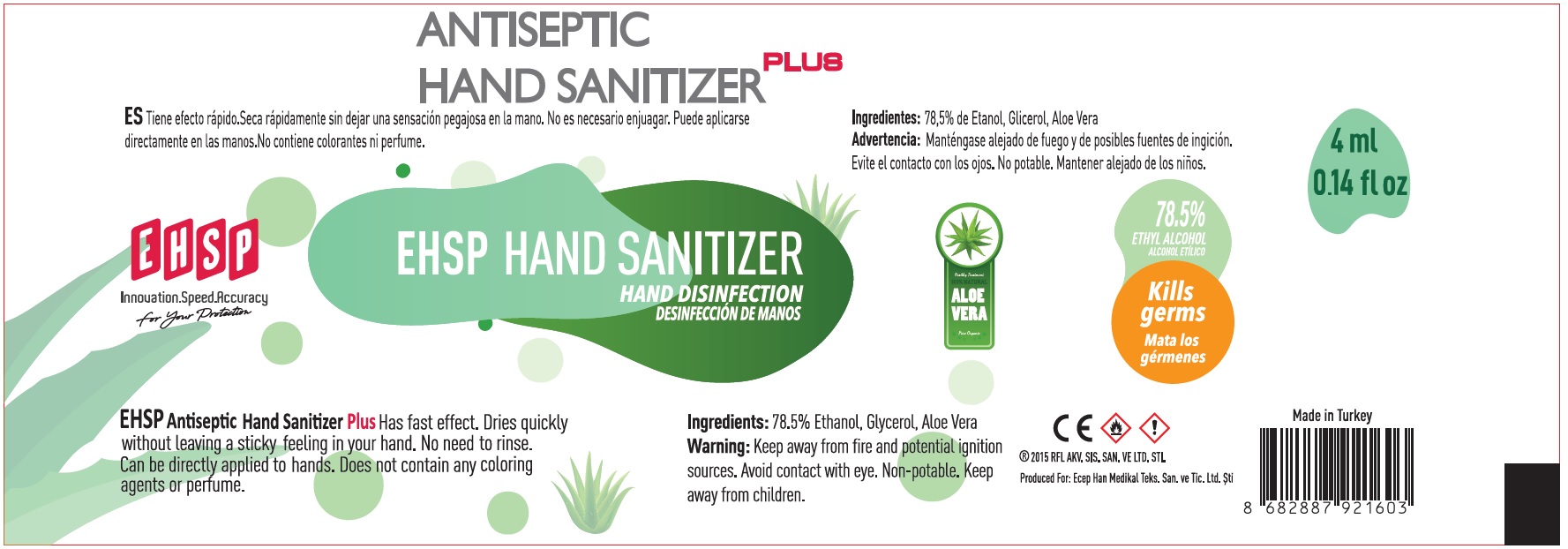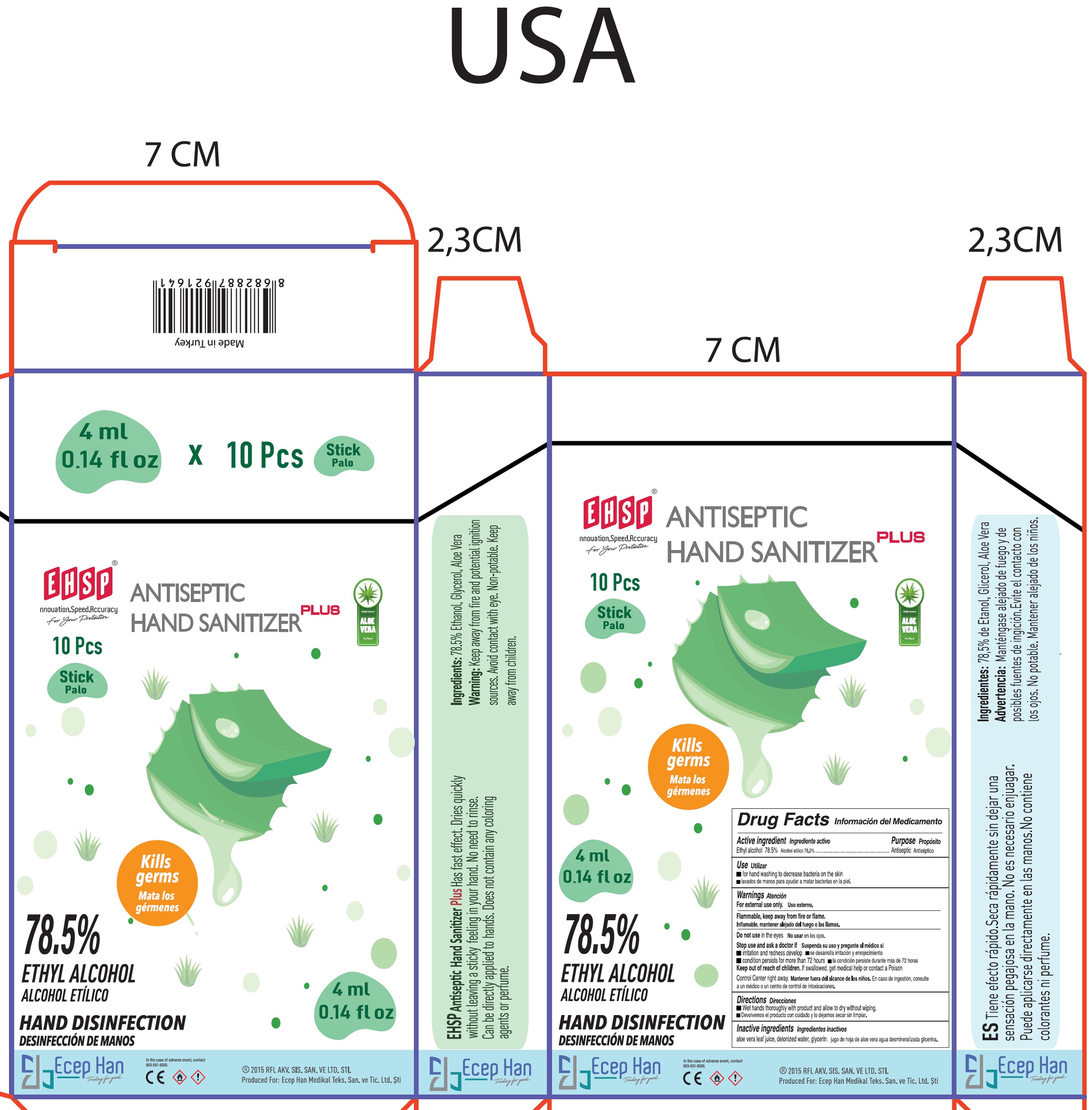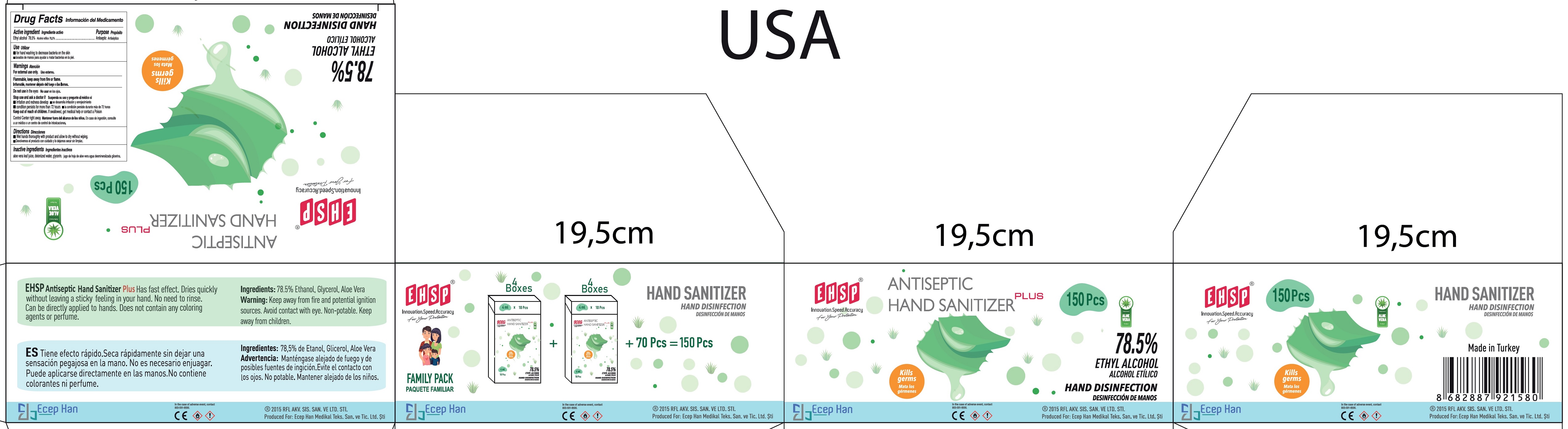 DRUG LABEL: EHSP hand sanitizer family pack
NDC: 82006-003 | Form: KIT | Route: TOPICAL
Manufacturer: ECEP HAN MEDIKAL TEKSTIL SANAYI VE TICARET LIMITED SIRKETI
Category: otc | Type: HUMAN OTC DRUG LABEL
Date: 20210804

ACTIVE INGREDIENTS: ALCOHOL 78.5 mL/100 mL; ALCOHOL 78.5 mL/100 mL
INACTIVE INGREDIENTS: ALOE VERA LEAF; WATER; GLYCERIN; ALOE VERA LEAF; WATER; GLYCERIN

EHSP hand sanitizer family pack

Active ingredient

Ethyl alcohol 78.5%

Purpose

Antiseptic

Use

- for hand washing to decrease bacteria on the skin

Warnings

For external use only.

Flammable, keep away from fire or flame.

Do not use

in the eyes

Stop use and ask a doctor if

- irritation and redness develop
- condition persists for more than 72 hours

Keep out of reach of children.

If swallowed, get medical help or contact a Poison Control Center right away.

Directions

- Wet hands thoroughly with product and allow to dry without wiping.

Inactive ingredients

aloe vera leaf juice, deionized water, glycerin.